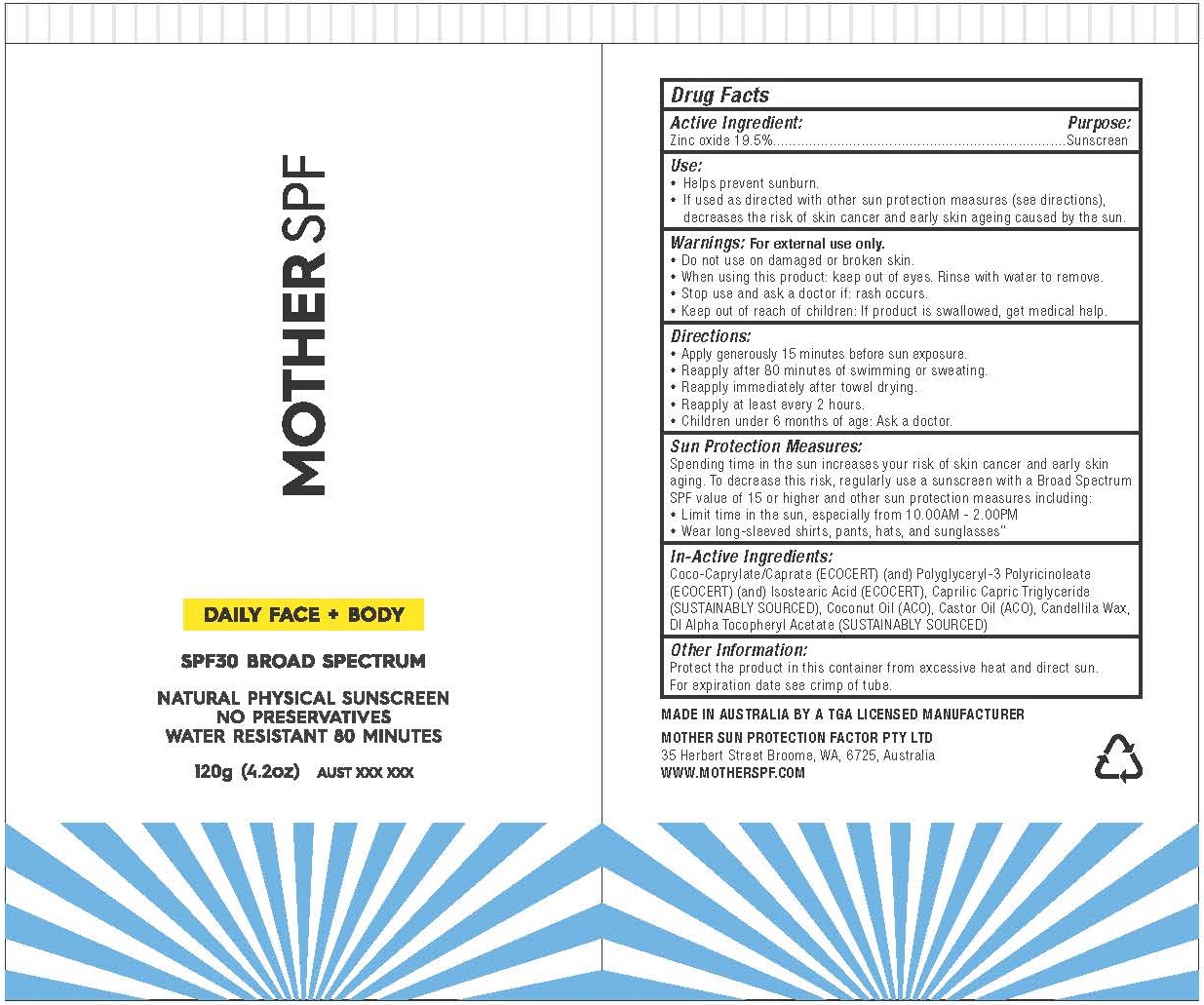 DRUG LABEL: MOTHER SPF - DAILY FACE AND BODY SPF30 BROAD SPECTRUM
NDC: 73204-101 | Form: LOTION
Manufacturer: MOTHER SUN PROTECTION FACTOR PTY LTD
Category: otc | Type: HUMAN OTC DRUG LABEL
Date: 20201231

ACTIVE INGREDIENTS: ZINC OXIDE 19.5 g/100 g
INACTIVE INGREDIENTS: COCO-CAPRYLATE/CAPRATE; POLYGLYCERYL-3 RICINOLEATE; Isostearic Acid; MEDIUM-CHAIN TRIGLYCERIDES; Coconut Oil; Castor Oil; CANDELILLA WAX; .ALPHA.-TOCOPHEROL ACETATE, DL-

MOTHER SPF - DAILY FACE AND BODY SPF30 BROAD SPECTRUM

ACTIVE INGREDIENT

ZINC OXIDE 19.5%

PURPOSE

SUNSCREEN

USE

- Helps prevent sunburn.
- If used as directed with other sun protection measures (see directions), decreases the risk of skin cancer and early skin ageing caused by the sun.

WARNINGS

For external use only.

- Do not use on damaged or broken skin.
- When using this product: keep out of eyes. Rinse with water to remove.
- Stop use and ask a doctor if: rash occurs.
- Keep out of reach of children: If product is swallowed, get medical help.

DIRECTIONS

- Apply generously 15 minutes before sun exposure.
- Reapply after 80 minutes of swimming or sweating.
- Reapply immediately after towel drying.
- Reapply at least every 2 hours.
- Children under 6 months of age: Ask a doctor.

SUN PROTECTION MEASURES

Spending time in the sun increases your risk of skin cancer and early skin aging. To decrease this risk, regularly use a sunscreen with a Broad Spectrum SPF value of 15 or higher and other sun protection measures including:

- Limit time in the sun, especially from 10.00AM - 2.00PM
- Wear long-sleeved shirts, pants, hats, and sunglasses”

INACTIVE INGREDIENTS

Coco-Caprylate/Caprate (ECOCERT) (and) Polyglyceryl-3 Polyricinoleate (ECOCERT) (and) Isostearic Acid (ECOCERT), Caprilic Capric Triglyceride (SUSTAINABLY SOURCED), Coconut Oil (ACO), Castor Oil (ACO), Candellila Wax, Dl Alpha Tocopheryl Acetate (SUSTAINABLY SOURCED)

OTHER INFORMATION

Protect the product in this container from excessive heat and direct sun.
For expiration date see crimp of tube.